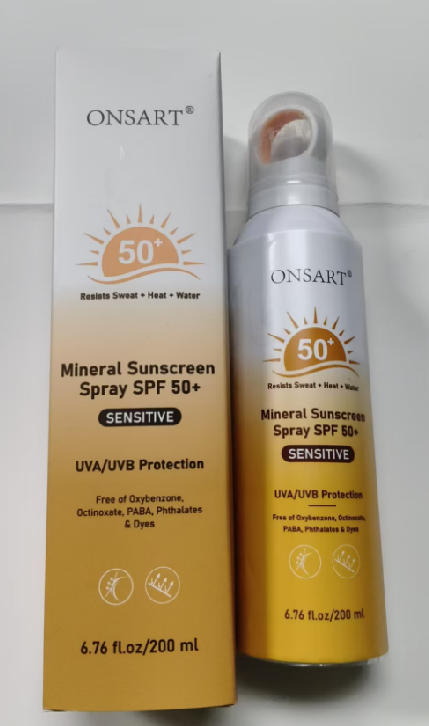 DRUG LABEL: ONSART Mineral Sunscreen SPF 50
NDC: 87204-160 | Form: SPRAY
Manufacturer: Guangzhou Huixue Biotechnology Co., Ltd.
Category: otc | Type: HUMAN OTC DRUG LABEL
Date: 20260127

ACTIVE INGREDIENTS: ZINC OXIDE 48 g/200 g
INACTIVE INGREDIENTS: PHENOXYETHANOL; ISOOCTANE; BUTYLENE GLYCOL; ALOE BARBADENSIS LEAF JUICE; DECYL GLUCOSIDE; SODIUM CHLORIDE; DIBUTYL ADIPATE; CAPRYLYL GLYCOL; ETHYLHEXYLGLYCERIN; WATER; ISOBUTANE; TOCOPHEROL; ZINC GLUCONATE; MAGNESIUM CHLORIDE; BISABOLOL; GLYCERIN; STEARIC ACID; CALCIUM GLUCONATE; POTASSIUM CHLORIDE; MAGNESIUM ASPARTATE; DIPOTASSIUM GLYCYRRHIZATE; HYALURONIC ACID; COPPER GLUCONATE; XANTHAN GUM

ACTIVE INGREDIENT

Zinc Oxide 24%

INACTIVE INGREDIENT

ALOE BARBADENSIS LEAF JUICE, DIBUTYL ADIPATE, ISOOCTANE, LAURYL PEG-10 TRIS(TRIMETHYLSILOXY)SILYLETHYL DIMETHICONE, POLYHYDROXYSTEARIC ACID, DECYL GLUCOSIDE, PHENOXYETHANOL, TOCOPHEROL, BISABOLOL, SILICA, BUTYLENE GLYCOL, ETHYLHEXYLGLYCERIN, DIPOTASSIUM GLYCYRRHIZATE, STEARIC ACID, PROPYLENE GLYCOL, XANTHAN GUM, OPUNTIA DILLENII EXTRACT, OPHIOPOGON JAPONICUS ROOT EXTRACT, AVENA SATIVA BRAN EXTRACT, PAEONIA ALBIFLORA ROOT EXTRACT, SCUTELLARIA BAICALENSIS ROOT EXTRACT, GREEN TEA （CAMELLIA SINENSIS）EXTRACT, WATER, HYALURONIC ACID, CAPRYLYL GLYCOL, ISOBUTANE, TOCOPHERYL ACETATE, GLYCERIN, COPPER GLUCONATE, SODIUM CHLORID, POTASSIUM CHLORIDE, MAGNESIUM CHLORIDE, CALCIUM GLUCONATE, ZINC GLUCONATE, CERAMIDE, MAGNESIUM ASPARTATE.

PURPOSE

Sunscreen

INDICATIONS AND USAGE

Helps prevent sunburn. If used as directed with other sun protection measures (see Directions), decreases the risk of skin cancer and early skin aging caused by the sun.

WARNINGS

For external use only. . Danger. Flammable. Contents under pressure. . Do not use near fire, heat or while smoking. Do not puncture or incinerate. Store at temperatures below 120°F (48°C). Do not use on damaged or broken skin. . When using this product, keep out of eyes. If contact occurs, rinse thoroughly with water. Stop use and ask a doctor if rash occurs. Keep out of reach of children. If swallowed, get medical help or contact a Poison Control Center right away. Use only as directed. Intentional misuse by deliberately concentrating and inhaling the contents can be harmful or fatal.

KEEP OUT OF REACH OF CHILDREN

If swallowed, get medical help or contact a Poison Control Center right away.

WHEN USING

Shake well before each use. Spray liberally and spread evenly by hand 15 minutes before sun exposure. Hold container 4 to 6 inches from the skin to apply.Rub in. Do not apply in windy conditions . Use in a well-ventilated area. Reapply: Reapply immediately after 80 minutes of swimming, sweating, or towel drying. Reapply at least every 2 hours. . Sun Protection Measures: Spending time in the sun increases your risk of skin cancer and early skin aging. To decrease this risk, regularly use a sunscreen with a Broad Spectrum SPF value of 15 or higher and other sun protection measures including : Limit time in the sun, especially from 10 a.m.-2 p.m. Wear long-sleeve shirts, pants, hats, and sunglasses. Children under 6 months: Ask a doctor.

Do not use near fire, heat or while smoking. Do not puncture or incinerate. Store at temperatures below 120°F (48°C). • Do not use on damaged or broken skin. . When using this product, keep out of eyes. If contact occurs, rinse thoroughly with water

STOP USE

Chest pain, rapid heart beat, faintness, or dizziness occurs sudden, unexplained weight gain occurs,your hands or feet swell.

DOSAGE AND ADMINISTRATION

Shake well before each use. Spray liberally and spread evenly by hand 15 minutes before sun exposure. Hold container 4 to 6 inches from the skin to apply.Rub in. Do not apply in windy conditions. Use in a well-ventilated area. Reapply: Reapply immediately after 80 minutes of swimming, sweating, or towel drying. Reapply at least every 2 hours. • Sun Protection Measures: Spending time in the sun increases your risk of skin cancer and early skin aging. To decrease this risk, regularly use a sunscreen with a Broad Spectrum SPF value of 15 or higher and other sun protection measures including: . Limit time in the sun, especially from 10 a.m.-2 p.m. Wear long-sleeve shirts, pants, hats, and sunglasses. Children under 6 months: Ask a doctor.